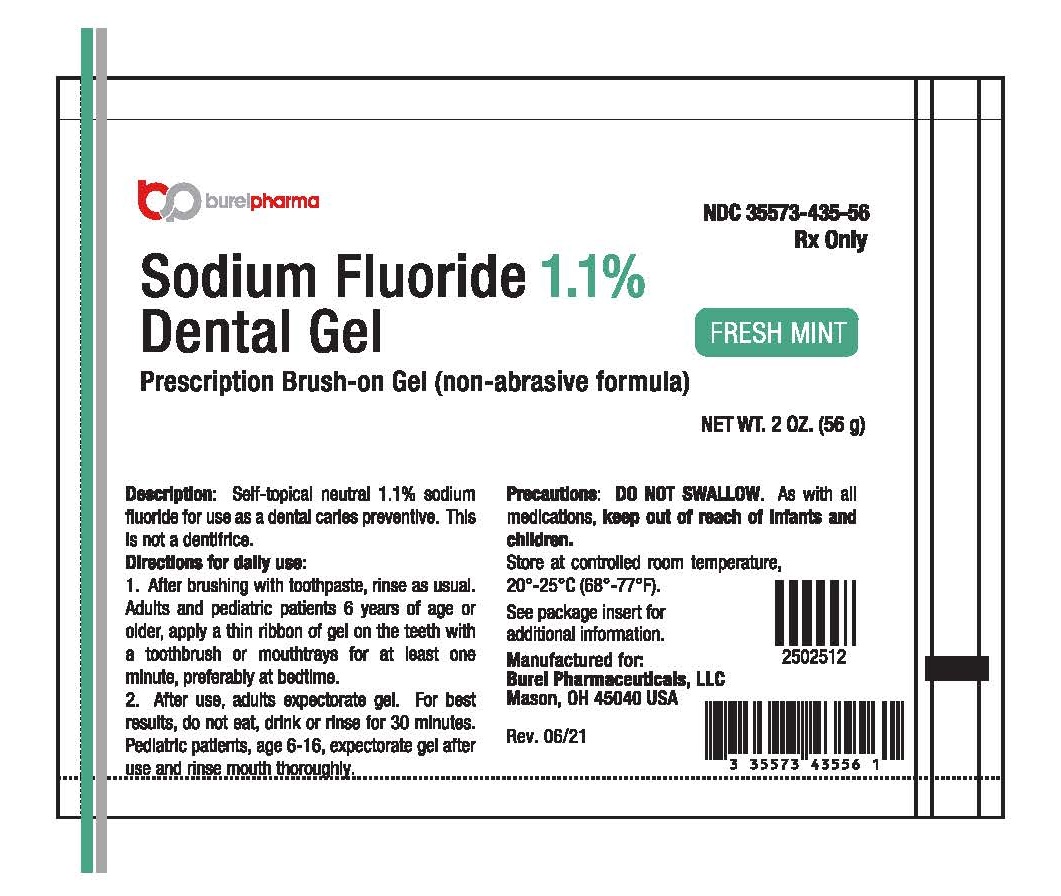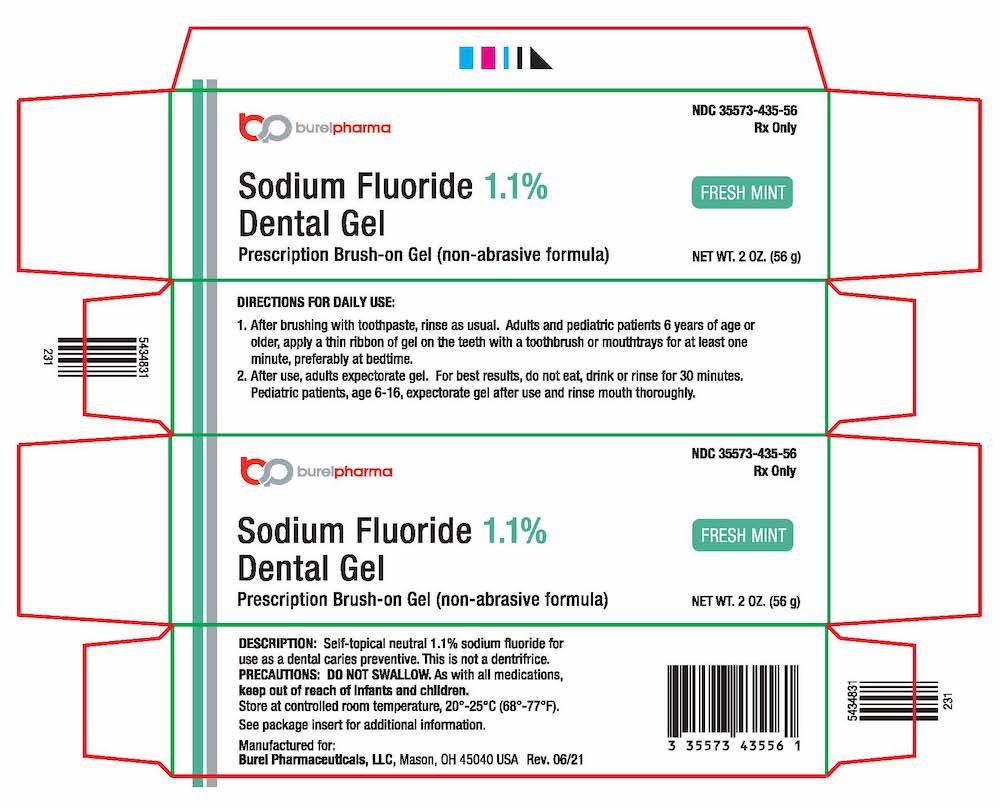 DRUG LABEL: Sodium Fluoride 1.1%
NDC: 35573-435 | Form: GEL, DENTIFRICE
Manufacturer: Burel Pharmaceuticals LLC
Category: prescription | Type: HUMAN PRESCRIPTION DRUG LABEL
Date: 20251114

ACTIVE INGREDIENTS: SODIUM FLUORIDE 5 mg/1 g
INACTIVE INGREDIENTS: WATER; SORBITOL; HYDROXYETHYL CELLULOSE (2000 CPS AT 1%); POLOXAMER 407; SACCHARIN SODIUM; METHYLPARABEN; PROPYLPARABEN; FD&C BLUE NO. 1

SODIUM FLUORIDE 1.1%
DENTAL GEL

SODIUM FLUORIDE 1.1% Prescription Dental Gel

DESCRIPTION:

Self-topical neutral fluoride gel containing 1.1% (w/v) sodium fluoride for use as a dental caries preventative in pediatric patients and adults. This prescription is not a dentifrice.

Active Ingredient:

Sodium Fluoride 1.1% (w/v)

Inactive Ingredients:

water (purified), sorbitol, hydroxyethylcellulose, flavor, poloxamer 407, sodium saccharin, methylparaben, propylparaben, FD&C Blue No.1.

CLINICAL PHARMACOLOGY:

Frequent topical applications to the teeth with preparations having a relatively high fluoride content increase tooth resistance to acid dissolution and enhance penetration of the fluoride ion into tooth enamel.

INDICATIONS AND USAGE:

A dental caries preventive; for once daily self-applied topical use. It is well established that 1.1% sodium fluoride is safe and extraordinarily effective as a caries preventive when applied frequently with mouthpiece applicators.^1-4 Sodium Fluoride 1.1% Dental Gel in a squeeze-tube is easily applied onto a toothbrush. This prescription dental gel should be used once daily following use of your regular toothpaste unless otherwise instructed by your dental professional. May be used whether or not drinking water is fluoridated, since topical fluoride cannot produce fluorosis. (See WARNINGSfor exception.)

CONTRAINDICATIONS:

Do not use in pediatric patients under age 6 years unless recommended by a dentist or physician.

WARNINGS:

Prolonged daily ingestion may result in various degrees of dental fluorosis in pediatric patients under age 6 years, especially if the water fluoridation exceeds 0.6 ppm, since younger pediatric patients frequently can not perform the brushing process without significant swallowing. Use in pediatric patients under age 6 years requires special supervision to prevent repeated swallowing of dental gel, which could cause dental fluorosis. Read directions carefully before using.

Keep out of reach of infants and children.

PRECAUTIONS:

Not for systemic treatment. DO NOT SWALLOW.

Carcinogenesis, Mutagenesis, Impairment of Fertility:

In a study conducted in rodents, no carcinogenesis was found in male and female mice and female rats treated with fluoride at dose levels ranging from 4.1 to 9.1 mg/kg of body weight. Equivocal evidence of carcinogenesis was reported in male rats treated with 2.5 and 4.1 mg/kg of body weight. In a second study, no carcinogenesis was observed in rats, males or females, treated with fluoride up to 11.3 mg/kg of body weight. Epidemiological data provide no credible evidence for an association between fluoride, either naturally occurring or added to drinking water, and risk of human cancer. Fluoride ion is not mutagenic in standard bacterial systems. It has been shown that fluoride ion has potential to induce chromosome aberrations in cultured human and rodent cells at doses much higher than those to which humans are exposed. In vivodata are conflicting. Some studies report chromosome damage in rodents, while other studies using similar protocols report negative results. Potential adverse reproductive effects of fluoride exposure in humans have not been adequately evaluated. Adverse effects on reproduction were reported for rats, mice, fox, and cattle exposed to 100 ppm or greater concentrations of fluoride in their diet or drinking water. Other studies conducted in rats demonstrated that lower concentrations of fluoride (5 mg/kg of body weight) did not result in impaired fertility and reproductive capabilities.

Pregnancy:

Pregnancy Category B. It has been shown that fluoride crosses the placenta of rats, but only 0.01% of the amount administered is incorporated in fetal tissue. Animal studies (rats, mice, rabbits) have shown that fluoride is not a teratogen. Maternal exposure to 12.2 mg fluoride/kg of body weight (rats) or 13.1 mg/kg of body weight (rabbits) did not affect the litter size or fetal weight and did not increase the frequency of skeletal or visceral malformations. There are no adequate and well-controlled studies in pregnant women. However, epidemiological studies conducted in areas with high levels of naturally fluoridated water showed no increase in birth defects. Heavy exposure to fluoride during in utero development may result in skeletal fluorosis, which becomes evident in childhood.

Nursing Mothers:

It is not known if fluoride is excreted in human milk. However, many drugs are excreted in milk, and caution should be exercised when products containing fluoride are administered to a nursing woman. Reduced milk production was reported in farm-raised fox when the animals were fed a diet containing a high concentration of fluoride (98-137 mg/kg of body weight). No adverse effects on parturition, lactation, or offspring were seen in rats administered fluoride up to 5 mg/kg of body weight.

Pediatric Use:

The use of Sodium Fluoride 1.1% Dental Gel in pediatric age groups 6 to 16 years as a caries preventive is supported by pioneering clinical studies with 1.1% sodium fluoride gels in mouth trays in students age 11-14 years conducted by Englander, et al.^2-4Safety and effectiveness in pediatric patients below the age of 6 years have not been established. Please refer to the CONTRAINDICATIONSand WARNINGSsections.

ADVERSE REACTIONS:

Allergic reactions and other idiosyncrasies have been rarely reported. To report SUSPECTED ADVERSE REACTIONS, contact Sheffield Pharmaceuticals, LLC. at 1-800-222-1087 or FDA at 1-800-FDA-1088 or www.fda.gov/medwatch.

OVERDOSAGE:

Accidental ingestion of large amounts of fluoride may result in acute burning in the mouth and sore tongue. Nausea, vomiting, and diarrhea may occur soon after ingestion (within 30 minutes) and are accompanied by salivation, hematemesis, and epigastric cramping abdominal pain. These symptoms may persist for 24 hours. If less than 5 mg fluoride/kg body weight (i.e., less than 2.3 mg fluoride/lb body weight) have been ingested, give calcium (e.g., milk) orally to relieve gastrointestinal symptoms and observe for a few hours. If more than 5 mg fluoride/kg body weight (i.e., more than 2.3 mg fluoride/lb body weight) have been ingested, induce vomiting, give orally soluble calcium (e.g., milk, 5% calcium gluconate or calcium lactate solution) and immediately seek medical assistance. For accidental ingestion of more than 15 mg fluoride/kg of body weight (i.e., more than 6.9 mg fluoride/lb body weight), induce vomiting and admit immediately to a hospital facility. A treatment dose (a thin ribbon) of Sodium Fluoride 1.1% Dental Gel contains 2 mg fluoride. A 2 oz. tube contains 255 mg fluoride.

DOSAGE AND ADMINISTRATION:

Follow these instructions unless otherwise instructed by your dental professional:

1. Adults and pediatric patients 6 years of age or older, apply a thin ribbon of gel to the teeth with a toothbrush or mouth trays once daily for at least one minute, preferably at bedtime.
2. After use, adults expectorate gel. For best results, do not eat, drink, or rinse for 30 minutes. Pediatric patients, age 6-16, expectorate after use and rinse mouth thoroughly.

 | HOW SUPPLIED: | Fresh Mint
 | 2 oz. (56g) net wt. tube | NDC# 35573-435-56

STORAGE:

Store at Controlled Room Temperature, 20-25°C (68-77°F).

REFERENCES:

1. American Dental Association, Council on Dental Therapeutics, Fluoride compounds, In:Accepted Dental Therapeutics, Ed. 40, Chicago, ADA, 405-407 (1984).
2. H.R. Englander et al., Clinical Anticaries Effects of Repeated Topical Sodium Fluoride Application by Mouthpieces, JADA, 75, 638-644 (1967).
3. H.R. Englander et al., Residual Anticaries Effects of Repeated Topical Sodium Fluoride Application by Mouthpieces, JADA, 78, 783-787 (1969).
4. H.R. Englander et al., Incremental Rates of Dental Caries After Repeated Topical Sodium Fluoride Applications in Children with Lifelong Consumption of Fluoridated Water, JADA, 82, 354-358 (1971).

PRINCIPAL DISPLAY PANEL - 56 g Tube

burelpharma NDC 35573-435-56

Rx only

Sodium Fluoride 1.1%

Dental Gel

Prescription Brush-on Gel (non-abrasive formula)

FRESH MINT

NET WT. 2.0 OZ. (56 g)

PRINCIPAL DISPLAY PANEL - 56 g Carton

burelpharma NDC 35573-435-56

� Rx only

Sodium Fluoride 1.1%

Dental Gel

Prescription Brush-on Gel (non-abrasive formula)

FRESH MINT

NET WT 2.0 oz (56g)